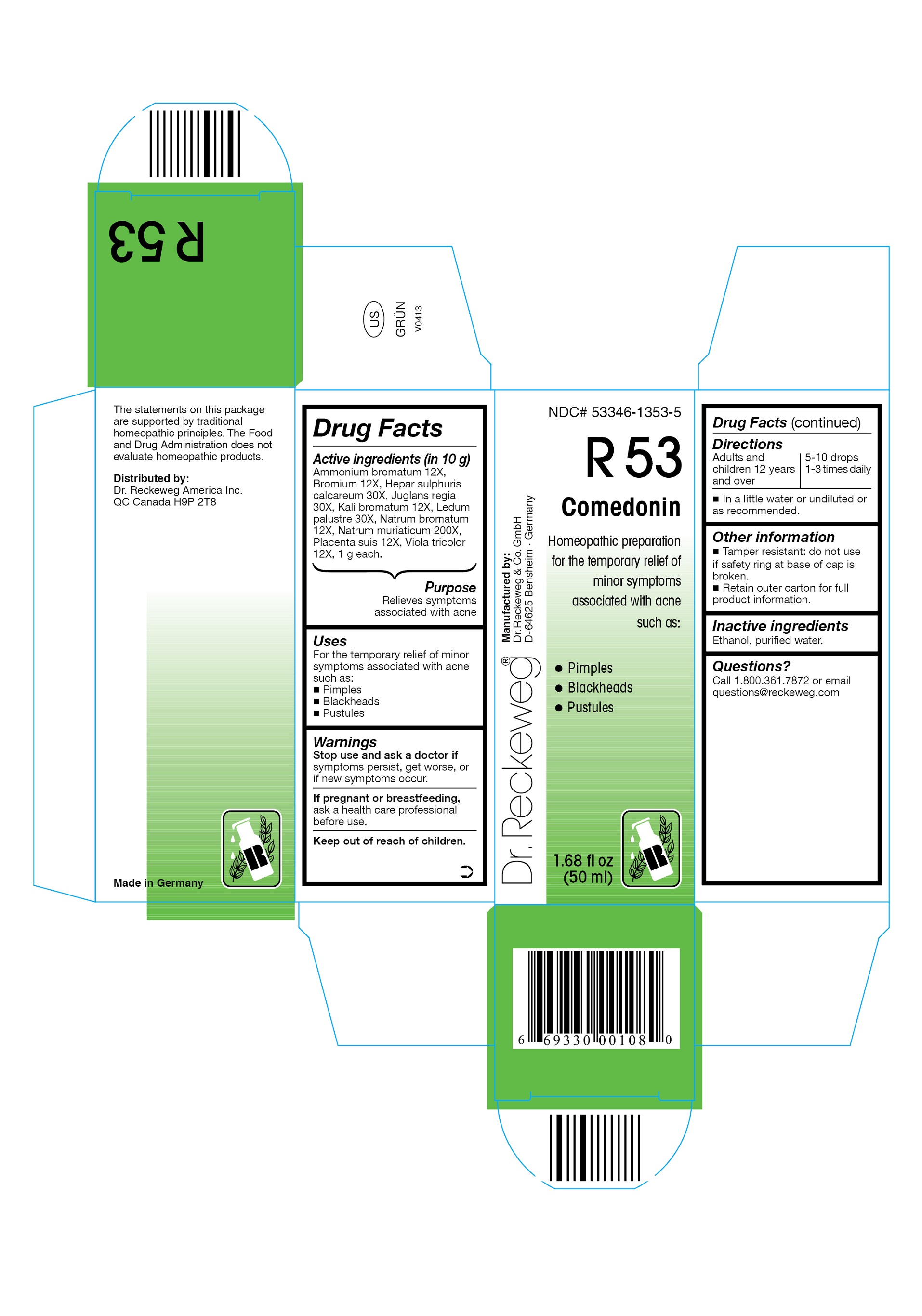 DRUG LABEL: DR. RECKEWEG R53 Comedonin
NDC: 53346-1353 | Form: LIQUID
Manufacturer: PHARMAZEUTISCHE FABRIK DR. RECKEWEG & CO
Category: homeopathic | Type: HUMAN OTC DRUG LABEL
Date: 20130404

ACTIVE INGREDIENTS: AMMONIUM BROMIDE 12 [hp_X]/50 mL; BROMINE 12 [hp_X]/50 mL; CALCIUM SULFIDE 30 [hp_X]/50 mL; ENGLISH WALNUT 30 [hp_X]/50 mL; POTASSIUM BROMIDE 12 [hp_X]/50 mL; LEDUM PALUSTRE TWIG 30 [hp_X]/50 mL; SODIUM BROMIDE 12 [hp_X]/50 mL; SODIUM CHLORIDE 200 [hp_X]/50 mL; SUS SCROFA PLACENTA 12 [hp_X]/50 mL; VIOLA TRICOLOR 12 [hp_X]/50 mL
INACTIVE INGREDIENTS: ALCOHOL; WATER

DR. RECKEWEG R53 Comedonin

Active ingredients

Ammonium bromatum 12X, Bromium 12X, Hepar sulphuris calcareum 30X, Juglans regia 30X, Kali bromatum 12X, Ledum palustre 30X, Natrum bromatum 12X, Natrum muriaticum 200X, Placenta suis 12X, Viola tricolor 12X, 1 g each in 10 g.

Purpose

Relieves symptoms associated with acne

Uses

For the temporary relief of minor symptoms associated with acne such as:

- Pimples
- Blackheads
- Pustules

Warnings

Stop use and ask a doctor if symptoms persist, get worse, or if new symptoms occur.

PREGNANCY OR BREAST FEEDING

If pregnant or breastfeeding, ask a health care professional before use.

Keep out of reach of children.

Directions

Adults and children ≥ 12 years 5-10 drops 1-3 times daily in a little water or undiluted or as recommended.

Other information

- Tamper resistant: do not use if safety ring at base of cap is broken.
- Retain outer carton for full product information.

Inactive ingredients

Ethanol, purified water.

Questions?

Call 1-800-361-7872 or email questions@reckeweg.com

PACKAGE LABEL

NDC# 53346-1353-5

Dr. Reckeweg R53 Comedonin

Homeopathic preparation for the temporary relief of minor symptoms associated with acne such as:

- Pimples
- Blackheads
- Pustules

Manufactured by:

Dr. Reckeweg Co. GmbH

D-64625 Bensheim

Germany

1.68 fl oz
(50 ml)